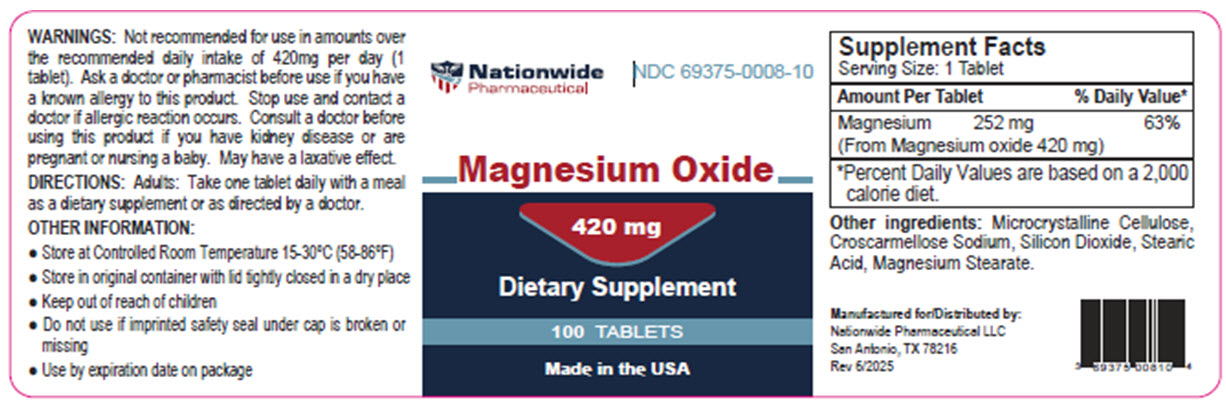 DRUG LABEL: Magnesium Oxide (Mg Supplement)
NDC: 69375-008 | Form: TABLET
Manufacturer: Nationwide Pharmaceutical LLC
Category: other | Type: DIETARY SUPPLEMENT
Date: 20250820

ACTIVE INGREDIENTS: MAGNESIUM OXIDE 420 mg/1 1
INACTIVE INGREDIENTS: MICROCRYSTALLINE CELLULOSE; CROSCARMELLOSE SODIUM; SILICON DIOXIDE; STEARIC ACID; MAGNESIUM STEARATE

MAGNESIUM OXIDE (MG SUPPLEMENT)- magnesium oxide tablet Nationwide Pharmaceutical LLC

Dietary Supplement

Magnesium Oxide 420 mg

420mg Magnesium Oxide per day (1 tablet)

Inactive Ingredients Microcrystalline Cellulose, Croscarmellose Sodium, Silicon Dioxide, Stearic Acid, Magnesium Stearate.

HEALTH CLAIM

Magnesium Supplement

Warnings

Not recommended for use in amounts over the recommended daily intake of 420mg per day (1 tablet). Ask a doctor or pharmacist before use if you have a known allergy to this product. Stop use and contact a doctor if allergic reaction occurs. Consult a doctor before using this product if you have kidney disease or are pregnant or nursing a baby. May have a laxative effect.

Directions

Adults: Take one tablet daily with a meal as a dietary supplement or as directed by a doctor.

Other information

- Store at Controlled Room Temperature 15-30°C (58-86°F)
- Store in original container with lid tightly closed in a dry place
- Keep out of reach of children
- Do not use if imprinted safety seal under cap is broken or missing
- Use by expiration date on package

Supplement Facts Serving Size: 1 Tablet

Amount Per Tablet % Daily Value*

Magnesium 252 mg 63%

(From Magnesium oxide 420 mg)

* Percent Daily Values are based on a 2,000 calorie diet.

Manufactured for/Distributed by:

Nationwide Pharmaceutical LLC San Antonio, TX 78216

Rev 6/2025

PRINCIPAL DISPLAY PANEL - 420 mg Tablet Bottle Label

Nationwide Pharmaceutical

NDC 69375-0008-10

Magnesium Oxide 420 mg

Dietary Supplement 100 TABLETS

Made in the USA